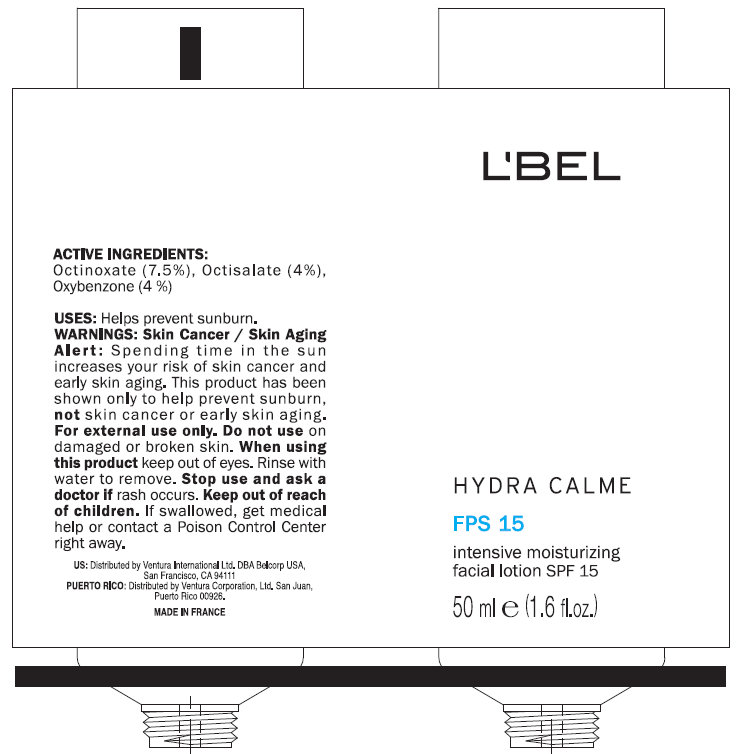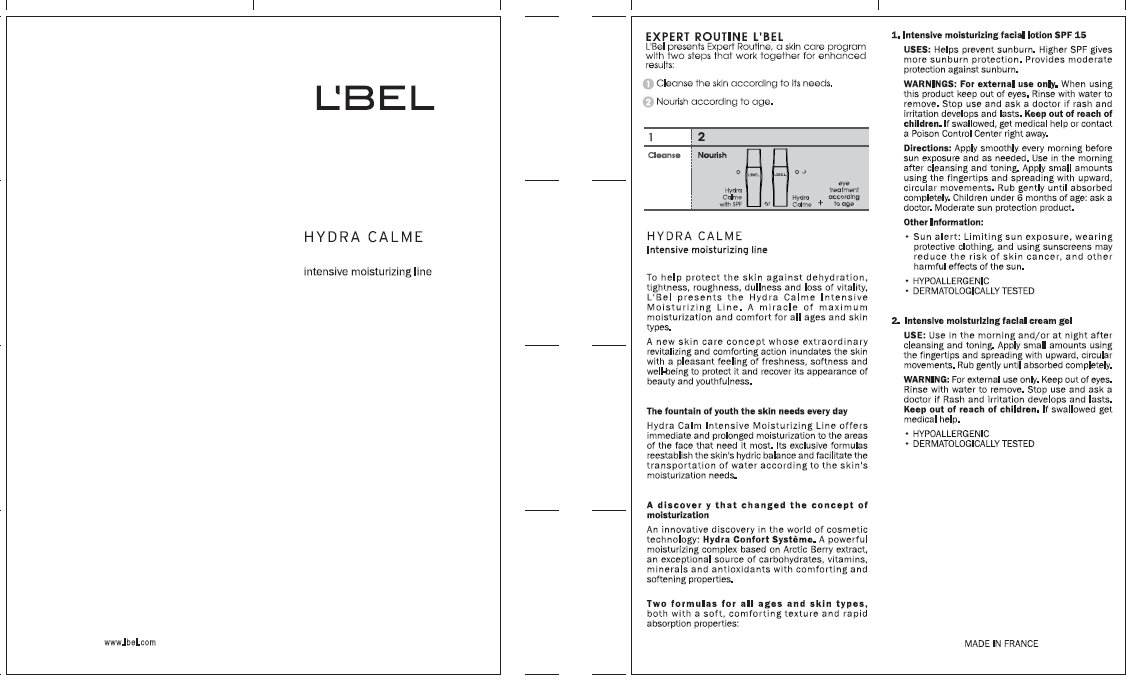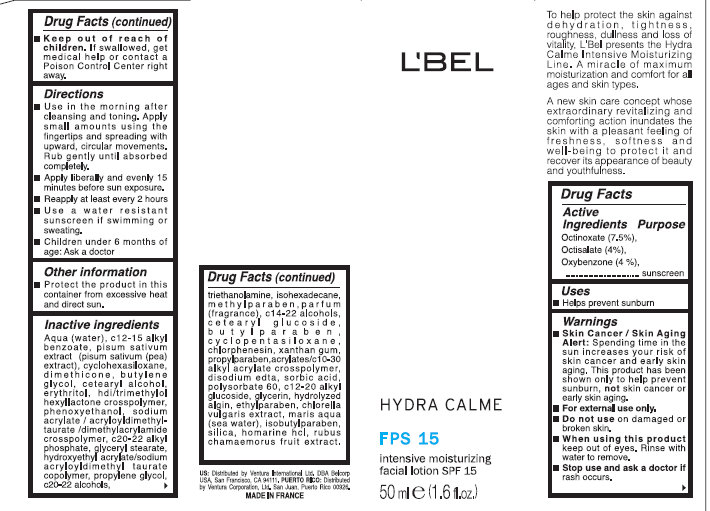 DRUG LABEL: LBEL HYDRA CALME SPF 15 Intensive Moisturizing Facial
NDC: 43455-0002 | Form: LOTION
Manufacturer: Ventura International, LTD
Category: otc | Type: HUMAN OTC DRUG LABEL
Date: 20120325

ACTIVE INGREDIENTS: OCTINOXATE 7.5 mL/100 mL; OCTISALATE 4 mL/100 mL; OXYBENZONE 4 mL/100 mL
INACTIVE INGREDIENTS: WATER; ALKYL (C12-15) BENZOATE; PEA; CYCLOMETHICONE 6; DIMETHICONE; BUTYLENE GLYCOL; CETOSTEARYL ALCOHOL; ERYTHRITOL; PHENOXYETHANOL; SODIUM ACRYLATE; C20-22 ALKYL PHOSPHATE; GLYCERYL MONOSTEARATE; SODIUM ACRYLATE/SODIUM ACRYLOYLDIMETHYLTAURATE COPOLYMER (4000000 MW); PROPYLENE GLYCOL; C20-22 ALCOHOLS; TROLAMINE; ISOHEXADECANE; METHYLPARABEN; C14-22 ALCOHOLS; CETEARYL GLUCOSIDE; BUTYLPARABEN; CYCLOMETHICONE 5; XANTHAN GUM; PROPYLPARABEN; EDETATE DISODIUM; SORBIC ACID; POLYSORBATE 60; C12-20 ALKYL GLUCOSIDE; GLYCERIN; ETHYLPARABEN; CHLORELLA VULGARIS; ISOBUTYLPARABEN; SILICON DIOXIDE; HOMARINE HYDROCHLORIDE; RUBUS CHAMAEMORUS FRUIT

L'BEL HYDRA CALME SPF 15 Intensive Moisturizing Facial Lotion

Active Ingredients

Octinoxate (7.5%),
Octisalate (4%),
Oxybenzone (4%)

Uses

- Helps prevent sunburn

Warnings

- Skin Cancer / Skin Aging Alert: Spending time in the sun increases your risk of skin cancer and early skin aging. This product has been shown only to help prevent sunburn, not skin cancer or early skin aging.
- For external use only.

Do not use

on damaged or broken skin.

When using this product

keep out of eyes. Rinse with water to remove.

Stop use and ask a doctor if

rash occurs.

Keep out of reach of children.

If swallowed, get medical help or contact a Poison Control Center right away.

Directions

- Use in the morning after cleansing and toning. Apply small amounts using the fingertips and spreading with upward, circular movements. Rub gently until absorbed completely.
- Apply liberally and evenly 15 minutes before sun exposure.
- Reapply at least every 2 years
- Use a water resistant sunscreen if swimming or sweating.
- Children under 6 months of age: Ask a doctor.

Other information

Aqua (water), c12-15 alkyl benzoate, pisum sativum extract (pisum sativum (pea) extract), cyclohexasiloxane, dimethicone, butylene glycol, cetearyl alcohol, erythritol, hdi/trimethylol hexyllactone crosspolymer, phenoxyethanol, sodium acrylate / acryloyldimethyl-taurate / dimethylacrylamide crosspolymer, c20-22 alkyl phosphate, glyceryl stearate, hydroxyethyl acrylate / sodium acryloyldimethyl taurate copolymer, propylene glycol, c20-22 alcohols, triethanolamine, isohexadecane, methylparaben, parfum (fragrance), c14-22 alcohols, cetearyl glucoside, butylparaben, cyclopentasiloxane, chlorphenesin, xanthan gum, propylparaben, acrylates/c10-20 alkyl acrylate crosspolymer, disodium edta, sorbic acid, polysorbate 60, c12-20 alkyl glucoside, glycerin, hydrolyzed algin, ethylparaben, chlorella vulgaris extract, maris aqua (sea water), isobutylparaben, silica, homarine hcl, rubus chamaemorus fruit extract.

Purpose

Sunscreen

EXPERT ROUTINE L'BEL

L'Bel presents Expert Routine, a skin care program with two steps that work together for enhanced results:

1. Cleanse the skin according to its needs
2. Nourish according to the age.

HYDRA CALME
Intensive moisturizing line
To help protect the skin against dehydration, tightness, roughness, dullness and loss of vitality. L'Bel presents the Hydra Calme Intensive Moisturizing Line. A miracle of maximum moisturization and comfort for all ages and skin types.
A new skin care concept whose extraordinary revitalizing and comforting action inundates the skin with a pleasant feeling of freshness, softness and wellbeing to protect it and recover its appearance of beauty and youthfulness.
The fountain of youth the skin needs every day
Hydra Calm Intensive Moisturizing Line offers immediate and prolonged moisturization to the areas of the face that need it most. Its exclusive formulas reestablish the skin's hydric balance and facilitate the transportation of water according to the skin's moisturization needs.
A discover that changed the concept of moisturization
An innovative discovery in the world of cosmetic technology: Hydra Comfort Systeme. A powerful moisturizing complex based on Arctic Berry Extract, an exceptional source of carbohydrates, vitamins, minerals and antioxidants with comforting and softening properties.
Two formulas for all ages and skin types, both with a soft, comforting texture and rapid absorption properties:
1. Intensive moisturizing facial lotion SPF 15
USES: Helps prevent sunburn. Higher SPF gives more sunburn protection. Provides moderate protection against sunburn.
WARNINGS: For external use only. When using this product keep out of eyes. Rinse with water to remove. Stop use and ask a doctor if rash and irritation develops and lasts. Keep out of reach of children. If swallowed, get medical help or contact a Poison Control Center right away.
Directions: Apply smoothly every morning before sun exposure and as needed. Use in the morning after cleansing and toning. Apply small amounts using fingertips and spreading with upward circular movements. Rub gently until absorbed completed. Children under 6 months of age: ask a doctor. Moderate sun protection product.
Other Information:

- Sun alert: Limiting sun exposure, wearing protective clothing, and using sunscreens may reduce the risk of skin cancer, and other harmful effects of the sun.
- HYPOALLERGENIC
- DERMATOLOGICALLY TESTED

2. Intensive moisturizing facial cream gel
USE: Use in the morning and / or at night after cleansing and toning. Apply small amounts using the fingertips and spreading with upward, circular movements. Rub gently until absorbed completely.
WARNING: For external use only. Keep out of eyes. Rinse with water to remove. Stop use and ask a doctor if Rash and irritation develops and lasts. Keep out of reach of children. If swallowed get medical help.

- HYPOALLERGENIC
- DERMATOLOGICALLY TESTED

WHEN USING

L'BEL HYDRA CALME FPS 15 intensive moisturizing facial lotion SPF 15 50 ml e (1.6 fl.oz.)

US: Dist. by Ventural Internationa Ltd. DBA Bellcorp USA, San Francisco, CA 94111
P.R. Dist. by Ventura Corporation Ltd., San Juan, Puerto Rico 00926 MADE IN FRANCE